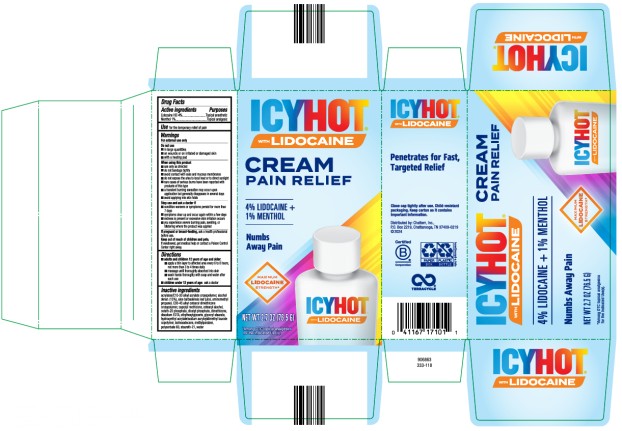 DRUG LABEL: Icy Hot with Lidocaine
NDC: 41167-1710 | Form: CREAM
Manufacturer: Chattem, Inc.
Category: otc | Type: HUMAN OTC DRUG LABEL
Date: 20250101

ACTIVE INGREDIENTS: LIDOCAINE 0.4 g/1 g; MENTHOL 0.1 g/1 g
INACTIVE INGREDIENTS: ALCOHOL; ALOE VERA LEAF; AMINOMETHYLPROPANOL; C30-45 ALKYL CETEARYL DIMETHICONE CROSSPOLYMER; CAPRYLYL METHICONE; CETOSTEARYL ALCOHOL; CETETH-20 PHOSPHATE; DICETYL PHOSPHATE; DIMETHICONE; EDETATE DISODIUM; ETHYLHEXYLGLYCERIN; GLYCERYL STEARATE; HYDROXYETHYL ACRYLATE/SODIUM ACRYLOYLDIMETHYL TAURATE COPOLYMER (100000 MPA.S AT 1.5%); ISOHEXADECANE; METHYLPARABEN; POLYSORBATE 60; STEARETH-21; WATER; ACRYLATES/C10-30 ALKYL ACRYLATE CROSSPOLYMER (60000 MPA.S AT 1.0%)

Icy Hot Cream

ICY HOT® with LIDOCAINE

PAIN RELIEVING CREAM

Drug Facts

Active Ingredients

Lidocaine HCl 4%

Purposes

Topical anesthetic

Active Ingredients

Menthol 1 %

Purposes

Topical analgesic

Use

for the temporary relief of pain

Warnings

For external use only

Do not use

■ in large quantities

■ on wounds or on irritated or damaged skin

■ with a heating pad

When using this product

■ use only as directed

■ do not bandage tightly

■ avoid contact with eyes and mucous membranes

■ do not expose the area to local heat or to direct sunlight

■ rare cases of serious burns have been reported with products of this type

■ a transient burning sensation may occur upon application but generally disappears in several days

■ avoid applying into skin folds

Stop use and ask a doctor if

■ condition worsens or symptoms persist for more than 7 days

■ symptoms clear up and occur again within a few days

■ redness is present or excessive skin irritation occurs

■ you experience severe burning pain, swelling, or blistering where the product was applied

If pregnant or breast-feeding,

ask a health professional before use.

Keep out of reach of children and pets.

If swallowed, get medical help or contact a Poison Control Center right away.

Directions

■ adults and children 12 years of age and older:

■ apply a thin layer to affected area every 6 to 8 hours, not more than 3 to 4 times daily

■ massage until thoroughly absorbed into skin

■ wash hands thoroughly with soap and water after each use

■ children under 12 years of age: ask a doctor

Inactive ingredients

acrylates/C10-30 alkyl acrylate crosspolymer, alcohol denat. (15%), aloe barbadensis leaf juice, aminomethyl propanol, C30-45 alkyl cetearyl dimethicone crosspolymer, caprylyl methicone, cetearyl alcohol, ceteth-20 phosphate, dicetyl phosphate, dimethicone, disodium EDTA, ethylhexylglycerin, glyceryl stearate, hydroxyethyl acrylate/sodium acryloyldimethyl taurate copolymer, isohexadecane, methylparaben, polysorbate 60, steareth-21, water

Keep Carton As It Contains Important Information

Close cap tightly between uses.

PRINCIPAL DISPLAY PANEL

ICY HOT
MAX
LIDOCAINE
PAIN RELIEF CREAM
Net Wt 2.7 OZ (76.5 g)